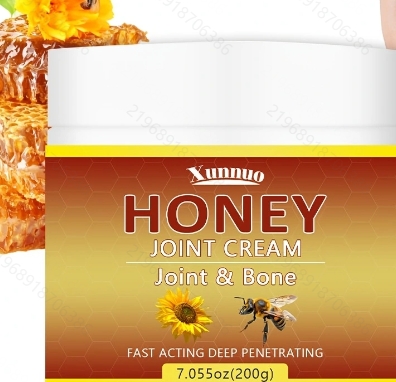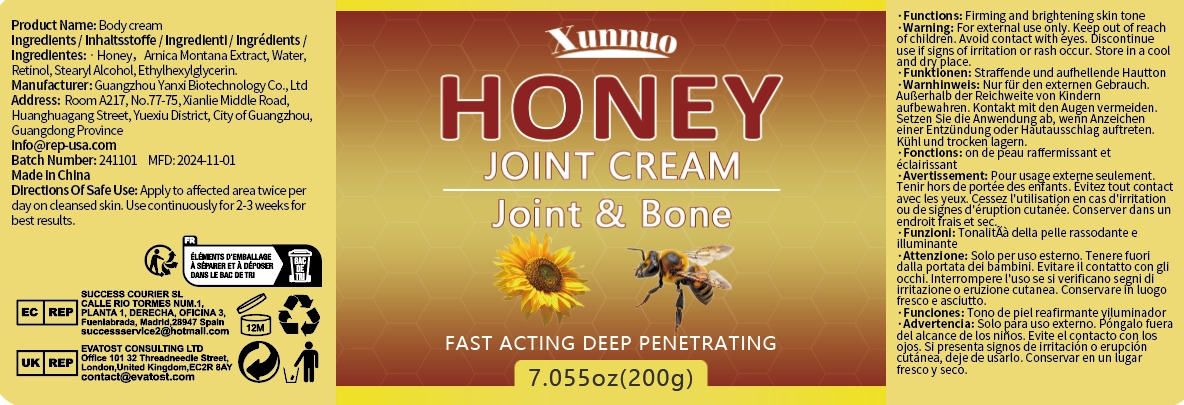 DRUG LABEL: Body cream
NDC: 84025-314 | Form: CREAM
Manufacturer: Guangzhou Yanxi Biotechnology Co., Ltd
Category: otc | Type: HUMAN OTC DRUG LABEL
Date: 20250107

ACTIVE INGREDIENTS: RETINOL 5 mg/200 g; HONEY 3 mg/200 g
INACTIVE INGREDIENTS: WATER

WARNINGS

Keep out of children

DOSAGE AND ADMINISTRATION

Apply to affected area twice perday on cleansed skin, Use continuously for2-3 weeks for best results.

INACTIVE INGREDIENT

Aqua

INDICATIONS AND USAGE

For daily skin care

Keep out of children

PURPOSE

Moisturizing skin